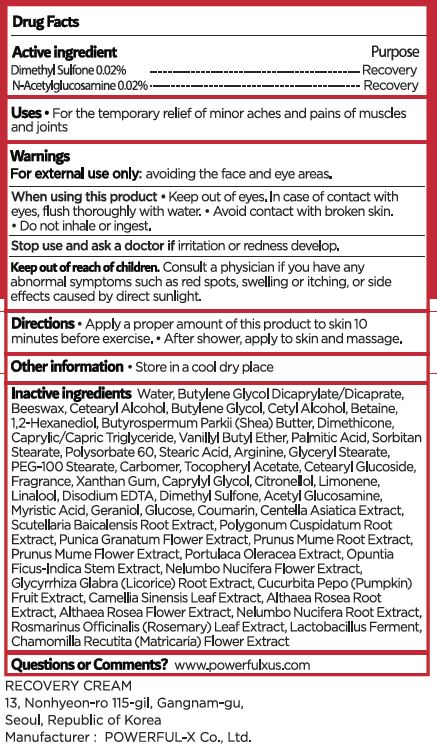 DRUG LABEL: PowerfulX RecoveryCream
NDC: 70042-0007 | Form: CREAM
Manufacturer: Power Fulx Co., Ltd.
Category: otc | Type: HUMAN OTC DRUG LABEL
Date: 20250109

ACTIVE INGREDIENTS: DIMETHYL SULFONE 0.02 g/100 mL; N-ACETYLGLUCOSAMINE 0.02 g/100 mL
INACTIVE INGREDIENTS: WATER; BUTYLENE GLYCOL

Drug Facts

ACTIVE INGREDIENT

Dimethyl Sulfone, N-Acetylglucosamine

INACTIVE INGREDIENT

Water, Butylene Glycol, etc

PURPOSE

Effection : Recovery and pain relief of minor aches and pains of muscles and joints

keep out of reach of the children

WARNINGS

- Warnings : For external use only: avoiding the face and eye areas.

DOSAGE AND ADMINISTRATION

Uses : For the temporary relief of minor aches and pains of muscles and joints

Directions :

ㆍApply a proper amount of this product to skin 10 minutes before exercise.

ㆍAfter shower, apply to skin and massage.